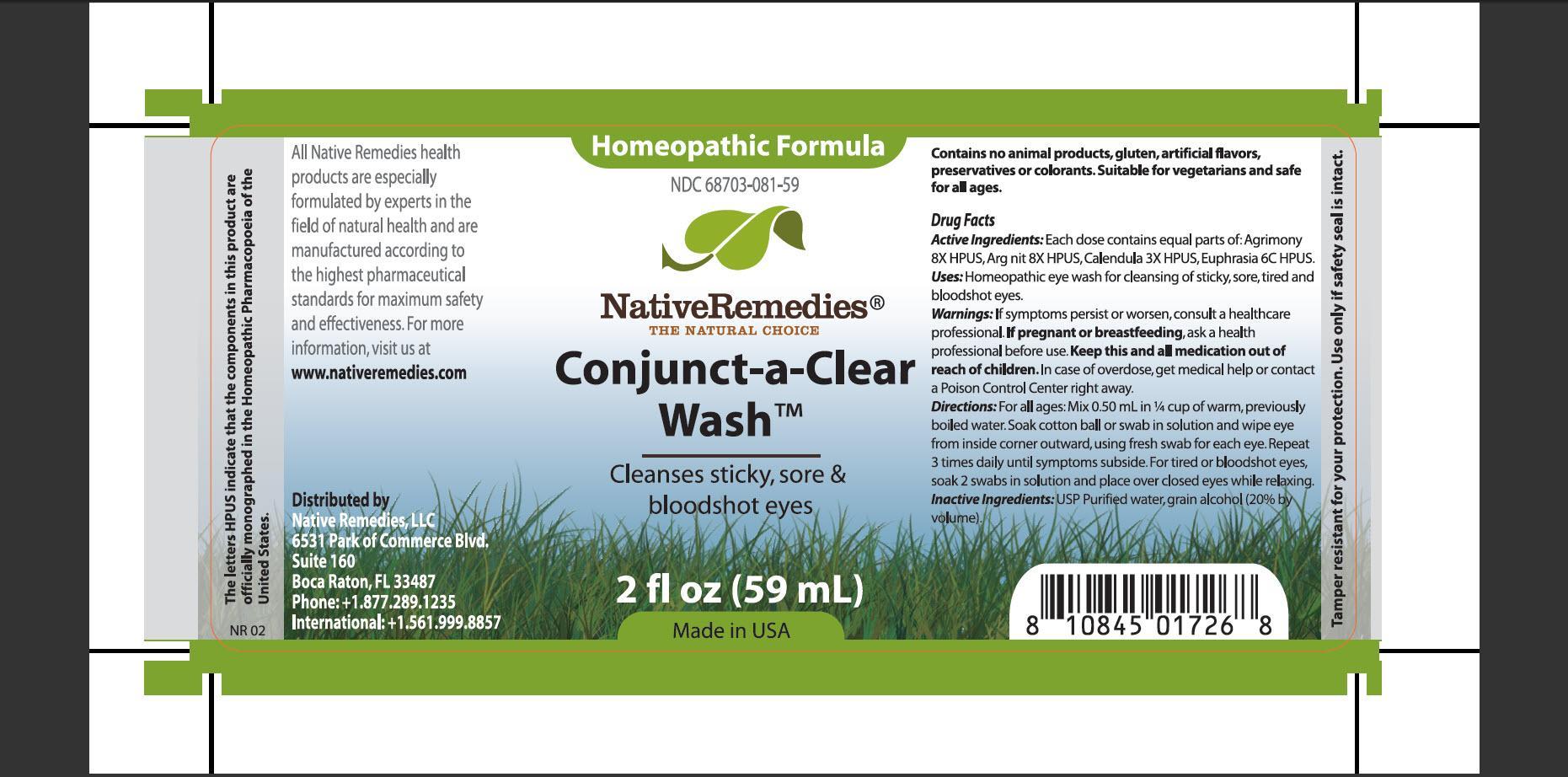 DRUG LABEL: Conjunct-a-Clear Wash
NDC: 68703-081 | Form: TINCTURE
Manufacturer: Native Remedies, LLC
Category: homeopathic | Type: HUMAN OTC DRUG LABEL
Date: 20130424

ACTIVE INGREDIENTS: AGRIMONIA EUPATORIA 8 [hp_X]/1 mL; SILVER NITRATE 8 [hp_X]/1 mL; CALENDULA OFFICINALIS FLOWERING TOP 3 [hp_X]/1 mL; EUPHRASIA STRICTA 6 [hp_C]/1 mL
INACTIVE INGREDIENTS: WATER; ALCOHOL

Conjunct-a-Clear Wash

PURPOSE

Cleanses sticky, sore and bloodshot eyes

ACTIVE INGREDIENT

Active Ingredients: Each dose contains equal parts of: Agrimony 8X HPUS, Arg nit 8X HPUS, Calendula 3X HPUS, Euphrasia 6C HPUS

INDICATIONS AND USAGE

Uses: Homeopathic eye wash for cleansing of stick, sore, tired and bloodshot eyes

WARNINGS

Warnings: If symptoms persist or worsen, consult a healthcare professional

PREGNANCY OR BREAST FEEDING

If pregnant or breastfeeding, ask a health professional before use

KEEP OUT OF REACH OF CHILDREN

Keep this and all medication out of reach of children

OVERDOSAGE

In case of overdose, get medical help or contact a Poison Control Center right away

DOSAGE AND ADMINISTRATION

Directions: For all ages: Mix 0.50 mL in 1/4 cup warm, previously boiled water. Soak cotton ball or swab in solution and wipe eye from inside corner outward, using fresh swab for each eye. Repeat 3 times daily until symptoms subside. For tired or bloodshot eyes, soak 3 swabs in solution and place over closed eyes while relaxing

INACTIVE INGREDIENT

Inactive Ingredients: USP Purified water, grain alcohol (20% by volume)

PATIENT COUNSELING INFORMATION

The letters HPUS indicate that the component in this product are officially monographed in the Homeopathic Pharmacopoeia of the United States

All Natives Remedies health products are especially formulated by experts in the field of natural health and are manufactured according to the highest pharmaceutical standards for maximum safety and effectiveness. For more information, visit us at www.nativeremedies.com

Distributed by
Native Remedies, LLC
6531 Park of Commerce Blvd.
Suite 160
Boca Raton, FL 33487
Phone: +1.877.289.1235
International:+1.561.999.8857

Contains no animal products, gluten, artificial flavors, preservatives or colorants. Suitable for vegetarians and safe for all ages

STORAGE AND HANDLING

Tamper resistant for your protection. Use only if safety seal is intact